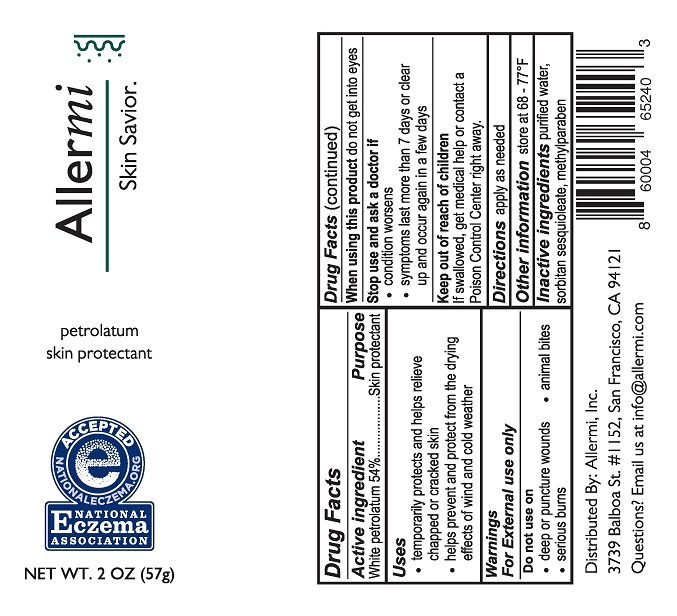 DRUG LABEL: Allermi Skin Savior
NDC: 81189-101 | Form: CREAM
Manufacturer: Allermi, Inc.
Category: otc | Type: HUMAN OTC DRUG LABEL
Date: 20220114

ACTIVE INGREDIENTS: PETROLATUM 54 g/100 g
INACTIVE INGREDIENTS: METHYLPARABEN; SORBITAN SESQUIOLEATE; WATER

Allermi Skin Savior

Drug Facts

Active ingredient

White petrolatum 54%

Purpose

Skin protectant

Uses

- temporarily protects and helps relieve chapped or cracked skin
- helps prevent and protect from the drying effects of wind and cold weather

Warnings

For External use only

Do not use on

- deep or puncture wounds
- animal bites
- serious burns

When using this product do not get into eyes

Stop use and ask a doctor if

- condition worsens
- symptoms last more than 7 days or clear up and occur again in a few days

Keep out of reach of children.

If swallowed, get medical help or contact a Poison Control Center right away.

DOSAGE AND ADMINISTRATION

Directions apply as needed

Other information store at 68 - 77°F

INACTIVE INGREDIENT

Inactive ingredients purified water, sorbitan sesquioleate, methylparaben

Distributed By: Allermi, Inc.

3739 Balboa St. #1152, San Francisco, CA 94121

Questions? Email us at info@allermi.com

PACKAGE LABEL

Allermi

Skin Savior

petrolatum

skin protectant

NET WT. 2 OZ (57g)